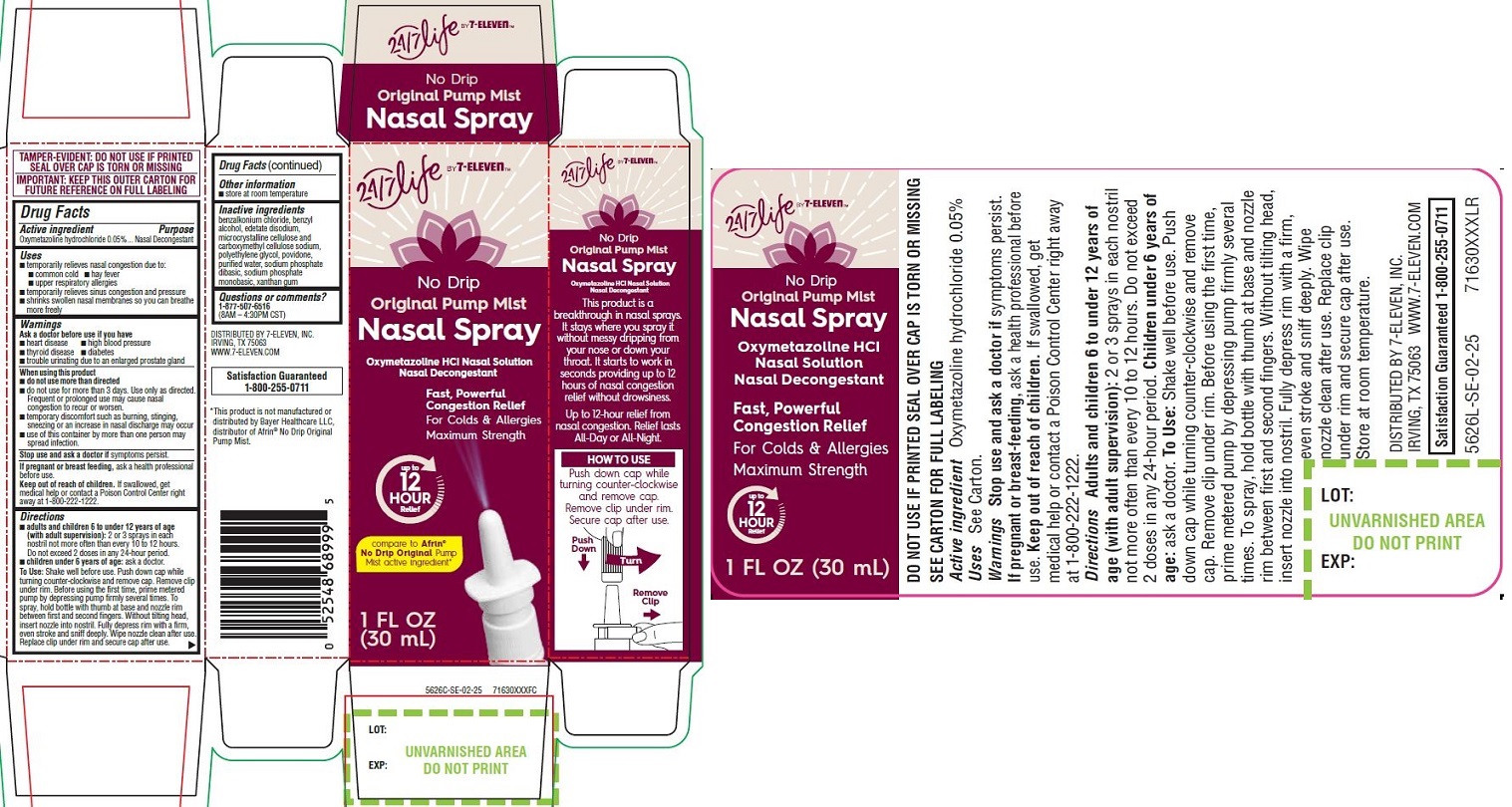 DRUG LABEL: Nasal Spray, 1oz, 24/7 Life by 7-Eleven
NDC: 66715-5526 | Form: SPRAY
Manufacturer: Lil' Drug Store Products, Inc.
Category: otc | Type: HUMAN OTC DRUG LABEL
Date: 20250930

ACTIVE INGREDIENTS: OXYMETAZOLINE HYDROCHLORIDE 0.05 g/100 mL
INACTIVE INGREDIENTS: SODIUM PHOSPHATE, MONOBASIC, UNSPECIFIED FORM; XANTHAN GUM; POVIDONE, UNSPECIFIED; SODIUM PHOSPHATE, DIBASIC, UNSPECIFIED FORM; MICROCRYSTALLINE CELLULOSE; EDETATE DISODIUM; POLYETHYLENE GLYCOL, UNSPECIFIED; WATER; CARBOXYMETHYLCELLULOSE SODIUM, UNSPECIFIED; BENZALKONIUM CHLORIDE; BENZYL ALCOHOL

Nasal Spray, 1oz, 24/7 Life by 7-Eleven

Drug Facts

Active ingredient

Oxymetazoline hydrochloride 0.05%

Purpose

Nasal Decongestant

Uses

- temporarily relieves nasal congestion due to:
- common cold
- hay fever
- upper respiratory allergies
- temporarily relieves sinus congestion and pressure
- shrinks swollen nasal membranes so you can breathe more freely

Warnings

Ask a doctor before use if you have

- heart disease
- high blood pressure
- thyroid disease
- diabetes
- trouble urinating due to an enlarged prostate gland

When using this product

- do not use more than directed
- do not use for more than 3 days. Use only as directed. Frequent or prolonged use may cause nasal congestion to recur or worsen.
- temporary discomfort such as burning, stinging, sneezing or an increase in nasal discharge may occur
- use of this container by more than one person may spread infection.

Stop use and ask a doctor ifsymptoms persist.

If pregnant or breast feeding,ask a health professional before use.

Keep out of reach of children.If swallowed, get medical help or contact a Poison Control Center right away at 1-800-222-1222.

Directions

- adults and children 6 to under 12 years of age (with adult supervision):2 or 3 sprays in each nostril not more often than every 10 to 12 hours. Do not exceed 2 doses in any 24-hour period.
- children under 6 years of age:ask a doctor.

To Use:Shake well before use. Push down cap while turning counter-clockwise and remove cap. Remove clip under rim. Before using the first time, prime metered pump by depressing pump firmly several times. To spray, hold bottle with thumb at base and nozzle rim
between first and second fingers. Without tilting head, insert nozzle into nostril. Fully depress rim with a firm, even stroke and sniff deeply. Wipe nozzle clean after use. Replace clip under rim and secure cap after use.

Other information

- store at room temperature

Inactive ingredients

benzalkonium chloride, benzyl alcohol, edetate disodium, microcrystalline cellulose and carboxymethyl cellulose sodium, polyethylene glycol, povidone, purified water, sodium phosphate dibasic, sodium phosphate monobasic, xanthan gum

Questions or comments

1-877-507-6516
(8AM – 4:30PM CST)

PACKAGE LABEL

24/7 Life by 7-Eleven

No Drip

Original Pump Mist

Nasal Spray

Oxymetazoline HCI Nasal Solution
Nasal Decongestant
Fast, Powerful
Congestion Relief
For Colds & Allergies
Maximum Strength

up to

12

HOUR

Relief

compare to Afrin®
No Drip Original Pump
Mist active ingredient*

1 FL OZ

(30 mL)